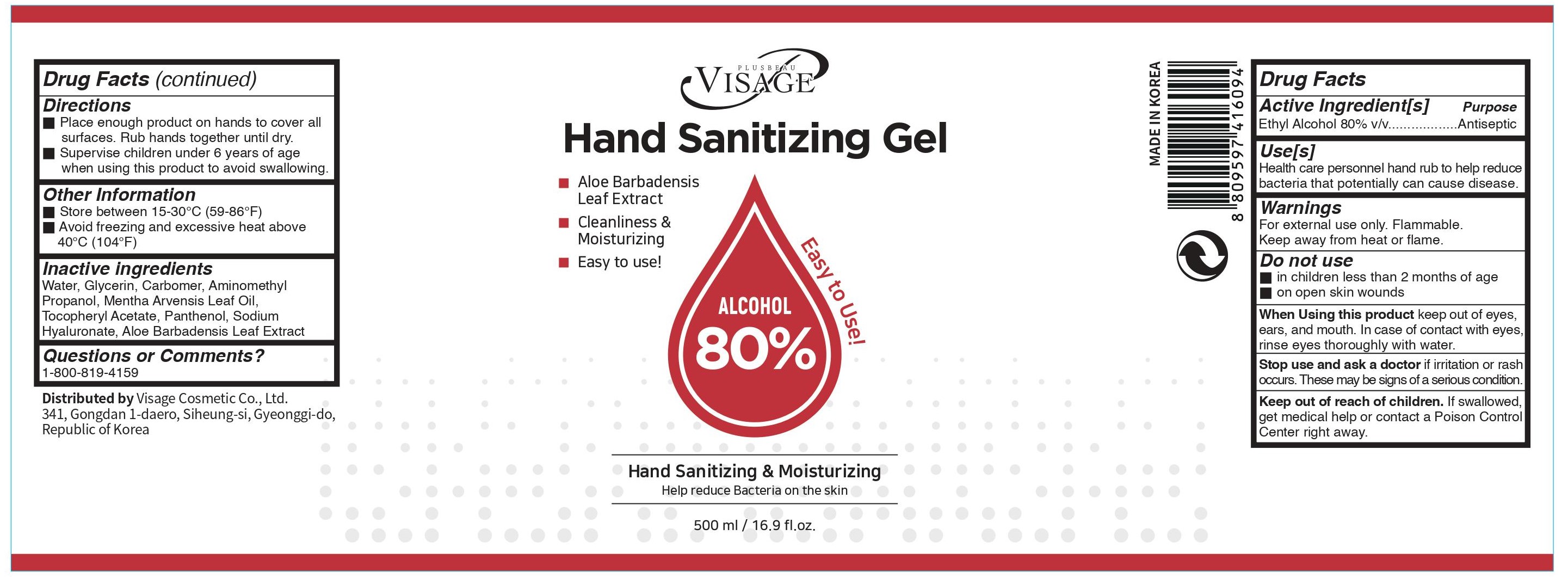 DRUG LABEL: PLUS BEAU VISAGE Hand Sanitizing Gel 80% 500ml
NDC: 74441-108 | Form: LIQUID
Manufacturer: Visage Cosmetic Co., Ltd
Category: otc | Type: HUMAN OTC DRUG LABEL
Date: 20200526

ACTIVE INGREDIENTS: ALCOHOL 80 mL/100 mL
INACTIVE INGREDIENTS: .ALPHA.-TOCOPHEROL ACETATE; ALOE VERA LEAF; MENTHA ARVENSIS LEAF OIL; PANTHENOL; HYALURONATE SODIUM; GLYCERIN; CARBOMER 940; WATER; AMINOMETHYLPROPANOL

PLUS BEAU VISAGE Hand Sanitizing Gel 80% 500ml

Active Ingredient(s)

Alcohol 80% v/v. Purpose: Antiseptic

Purpose

Antiseptic, Hand Sanitizer

Use

Health care personnel hand rub to help reduce bacteria that potentially can cause disease.

Warnings

For external use only. Flammable. Keep away from heat or flame

Do not use

- in children less than 2 months of age
- on open skin wounds

When using

When using this product keep out of eyes, ears, and mouth. In case of contact with eyes, rinse eyes thoroughly with water.

Stop use

Stop use and ask a doctor if irritation or rash occurs. These may be signs of a serious condition.

Keep out of reach of children. If swallowed, get medical help or contact a Poison Control Center right away.

Directions

- Place enough product on hands to cover all surfaces. Rub hands together until dry.
- Supervise children under 6 years of age when using this product to avoid swallowing.

Other information

- Store between 15-30C (59-86F)
- Avoid freezing and excessive heat above 40C (104F)

Inactive ingredients

Water, Glycerin, Carbomer, Aminomethyl Propanol, Mentha Arvensis Leaf Oil, Tocopheryl Acetate, Panthenol, Sodium Hyaluronate, Aloe Barbadensis Leaf Extract

Questions or Comments?

1-800-819-4159

Package Label - Principal Display Panel

PLUSBEAU VISAGE Hand Sanitizing Gel
Aloe Barbadensis Leaf Extract
Cleanliness & Moisturizing
Easy to use!
Alcohol 80%
Hand Sanitizing & Moisturizing
Help reduce Bacteria on the skin
500 mL / 16.9 fl. oz.